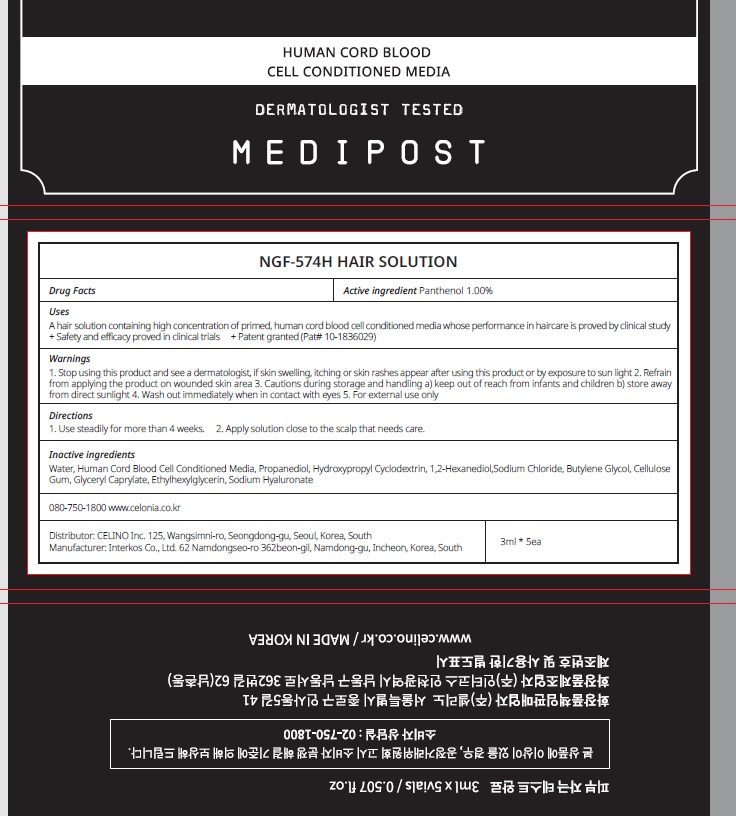 DRUG LABEL: NGF 574H HAIR
NDC: 73655-130 | Form: SOLUTION
Manufacturer: Celino Inc.
Category: otc | Type: HUMAN OTC DRUG LABEL
Date: 20211029

ACTIVE INGREDIENTS: Panthenol 1 g/100 mL
INACTIVE INGREDIENTS: Water; Propanediol

ACTIVE INGREDIENT

Panthenol 1.00%

INACTIVE INGREDIENTS

Water, Human Cord Blood Cell Conditioned Media, Propanediol, Hydroxypropyl Cyclodextrin, 1,2-Hexanediol,Sodium Chloride, Butylene Glycol, Cellulose Gum, Glyceryl Caprylate, Ethylhexylglycerin, Sodium Hyaluronate

PURPOSE

Hair growth

WARNINGS

1. Stop using this product and see a dermatologist, if skin swelling, itching or skin rashes appear after using this product or by exposure to sun light 2. Refrain from applying the product on wounded skin area 3. Cautions during storage and handling a) keep out of reach from infants and children b) store away from direct sunlight 4. Wash out immediately when in contact with eyes 5. For external use only

KEEP OUT OF REACH OF CHILDREN

keep out of reach from infants and children

Uses

A hair solution containing high concentration of primed, human cord blood cell conditioned media whose performance in haircare is proved by clinical study
+ Safety and efficacy proved in clinical trials
+ Patent granted (Pat# 10-1836029)

Directions

1. Use steadily for more than 4 weeks.
2. Apply solution close to the scalp that needs care.

QUESTIONS

080-750-1800 www.celonia.co.kr